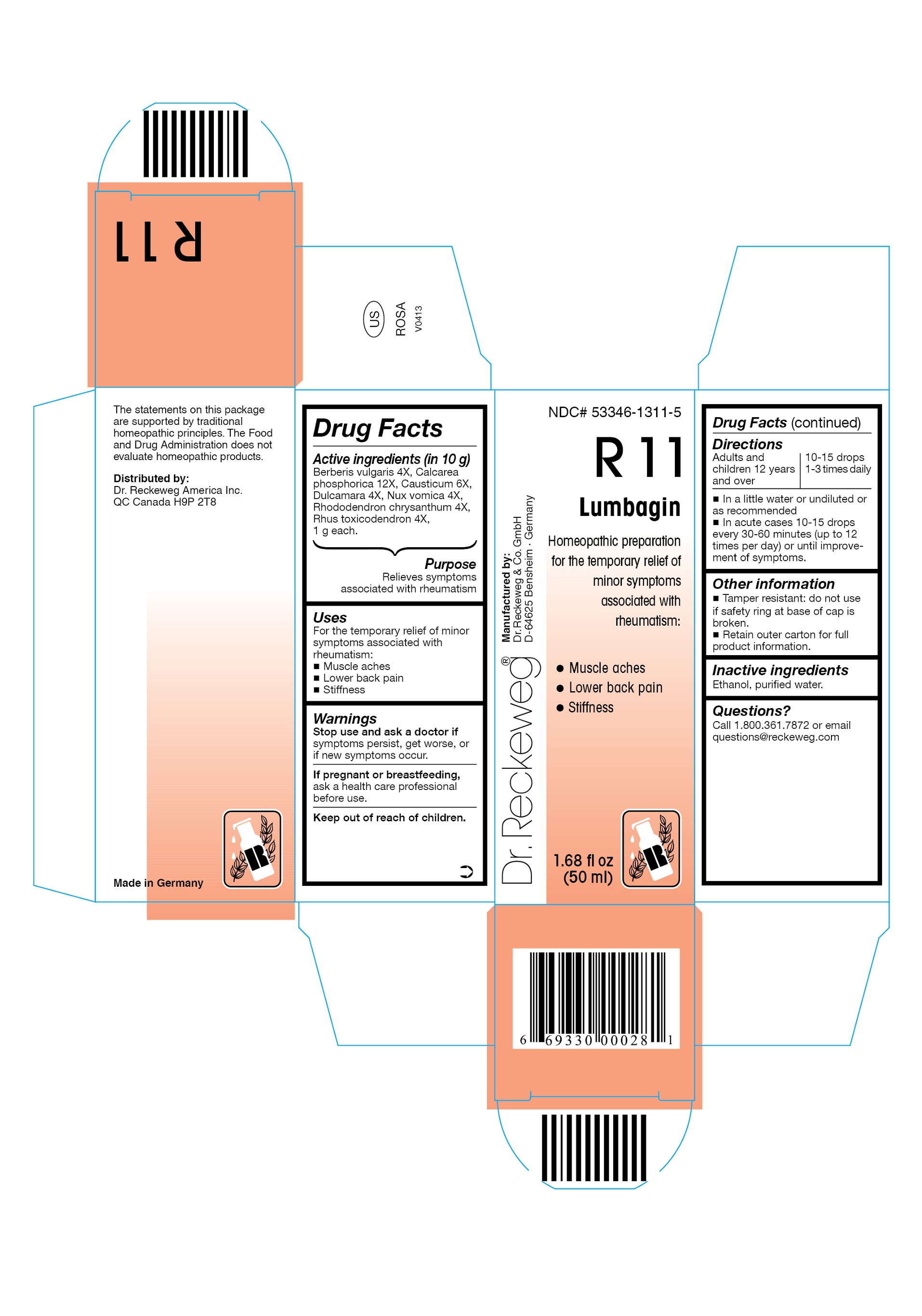 DRUG LABEL: DR. RECKEWEG R11 Lumbagin
NDC: 53346-1311 | Form: LIQUID
Manufacturer: PHARMAZEUTISCHE FABRIK DR. RECKEWEG & CO
Category: homeopathic | Type: HUMAN OTC DRUG LABEL
Date: 20130403

ACTIVE INGREDIENTS: BERBERIS VULGARIS ROOT BARK 4 [hp_X]/50 mL; CALCIUM PHOSPHATE, DIBASIC, DIHYDRATE 12 [hp_X]/50 mL; CAUSTICUM 6 [hp_X]/50 mL; SOLANUM DULCAMARA TOP 4 [hp_X]/50 mL; STRYCHNOS NUX-VOMICA SEED 4 [hp_X]/50 mL; RHODODENDRON AUREUM LEAF 4 [hp_X]/50 mL; TOXICODENDRON PUBESCENS LEAF 4 [hp_X]/50 mL
INACTIVE INGREDIENTS: ALCOHOL; WATER

DR. RECKEWEG R11 Lumbagin

Active ingredients

Berberis vulgaris 4X, Calcarea phosphorica 12X, Causticum 6X, Dulcamara 4X, Nux vomica 4X, Rhododendron chrysanthum 4X, Rhus toxicodendron 4X, 1 g each in 10 g.

Purpose

Relieves symptoms associated with rheumatism

Uses

For the temporary relief of minor symptoms associated with rheumatism:

- Muscle aches
- Lower back pain
- Stiffness

Warnings

Stop use and ask a doctor if symptoms persist, get worse, or if new symptoms occur.

PREGNANCY OR BREAST FEEDING

If pregnant or breastfeeding, ask a health care professional before use.

Keep out of reach of children.

Directions

Adults and children ≥ 12 years 10-15 drops 1-3 times daily;

acute cases 10-15 drops every 30-60 minutes (up to 12 times per day) or until improvement of symptoms, in a little water or undiluted or as recommended.

Other information

- Tamper resistant: do not use if safety ring at base of cap is broken.
- Retain outer carton for full product information.

Inactive ingredients

Ethanol, purified water.

Questions?

Call 1-800-361-7872 or email questions@reckeweg.com

PACKAGE LABEL

NDC# 53346-1311-5

Dr. Reckeweg R11 Lumbagin

Homeopathic preparation for the temporary relief of minor symptoms associated with rheumatism:

- Muscle aches
- Lower back pain
- Stiffness

Manufactured by:

Dr. Reckeweg Co. GmbH

D-64625 Bensheim

Germany

1.68 fl oz
(50 ml)